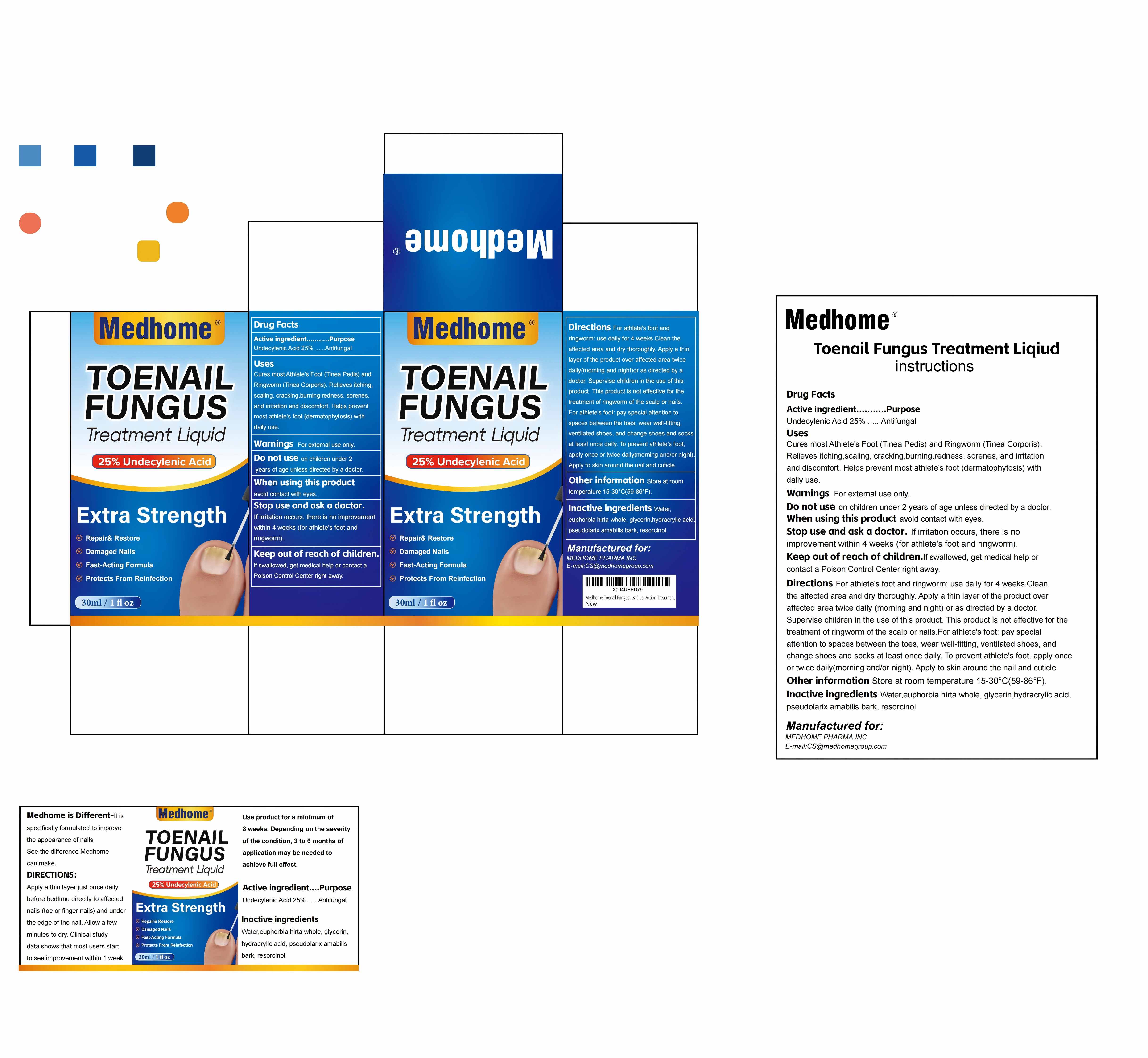 DRUG LABEL: FUNGAL NAIL RENEWAL
NDC: 84007-130 | Form: LIQUID
Manufacturer: Medhome Pharma Inc
Category: otc | Type: HUMAN OTC DRUG LABEL
Date: 20250929

ACTIVE INGREDIENTS: UNDECYLENIC ACID 25 g/100 mL
INACTIVE INGREDIENTS: PSEUDOLARIX AMABILIS BARK; GLYCERIN; HYDRACRYLIC ACID; WATER; EUPHORBIA HIRTA WHOLE; RESORCINOL

ACTIVE INGREDIENT

Undecylenic acid 25%

PURPOSE

Antifungal

Use

Cures most Athlete's Foot (Tinea Pedis)
and Ringworm (Tinea Corporis). Relieves
itching, scaling, cracking, burning,
redness, sorenes, and irritation and
discomfort. Helps prevent most athlete's
foot (dermatophytosis) with daily use.

WARNINGS

For external use only.

DO NOT USE

on children under 2 years
of age unless directed by a doctor.

WHEN USING

avoid contact with eyes.

STOP USE

irritation occurs, there is no improvement within 4 weeks (for athlete's foot and ringworm).

ASK DOCTOR

irritation occurs, there is no improvement
within 4 weeks (for athlete's foot and
ringworm).

KEEP OUT OF REACH OF CHILDREN

If swallowed, get medical help or contact a Poison Control Center right away.

INDICATIONS AND USAGE

For athlete's foot and ringworm: use daily for 4 weeks.

Clean theaffected area and dry thoroughly.

Apply a thin layer of the product over affected area twice daily (morning and night) or as directed by a doctor.

Supervise children in the use of this product.

This product is not effective for the treatment of ringworm of the scalp or nails.

For athlete's foot: pay special attention to spaces between the toes, wear well-fitting,

ventilated shoes, and change shoes and socks at least once daily.

To prevent athlete's foot, apply once or twice daily (morning and/or night).

Apply to skin around the nail and cuticle.

PATIENT COUNSELING INFORMATION

Store at room temperature 15-30℃ (59-86℉)

INACTIVE INGREDIENT

water, euphorbia hirta whole, glycerin, hydracrylic acid, pseudolarix amabilis bark, resorcinol.

DOSAGE AND ADMINISTRATION

30ml/1OZ